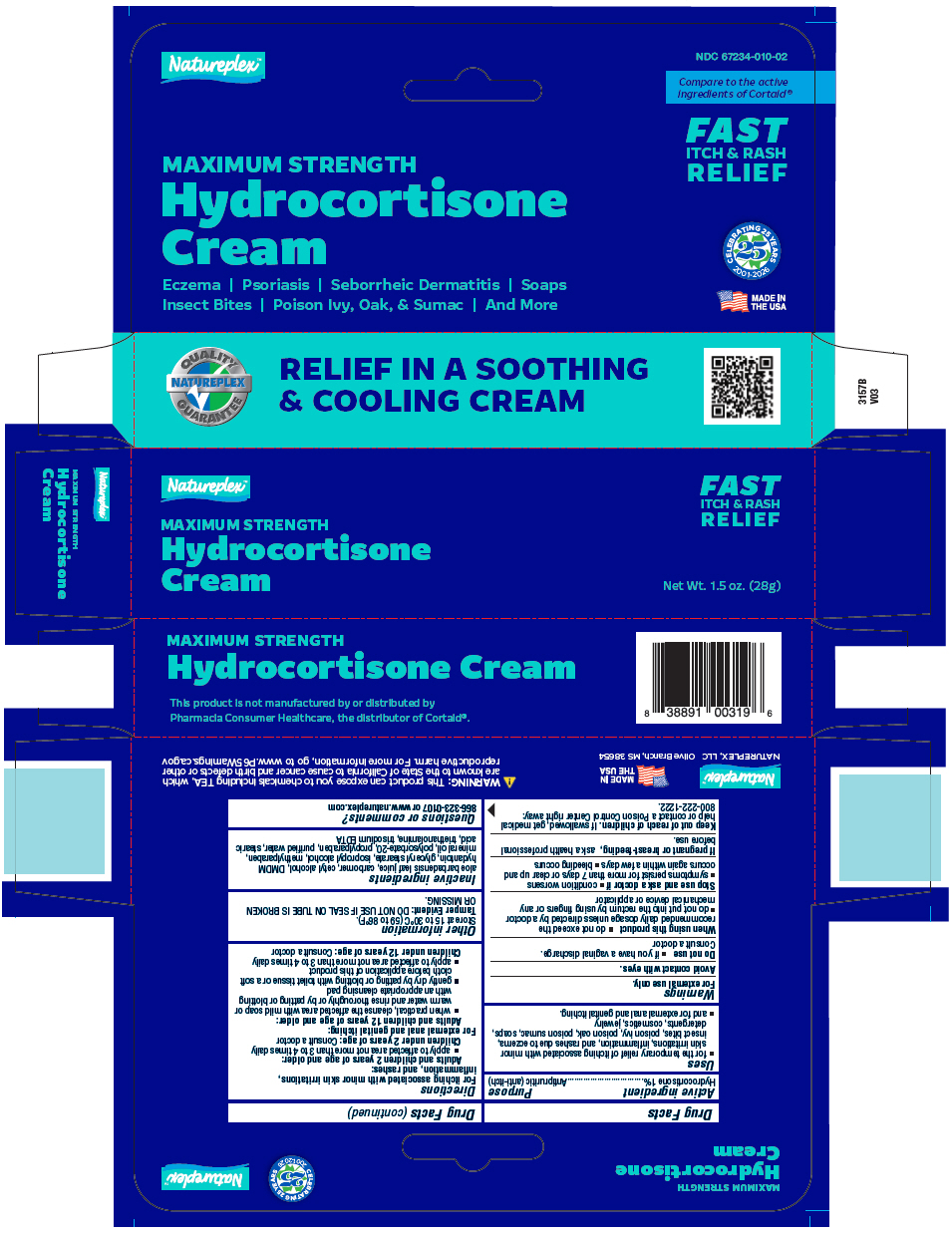 DRUG LABEL: Natureplex Hydrocortisone
NDC: 67234-010 | Form: CREAM
Manufacturer: Natureplex, LLC
Category: otc | Type: HUMAN OTC DRUG LABEL
Date: 20260213

ACTIVE INGREDIENTS: Hydrocortisone 0.01 g/1 g
INACTIVE INGREDIENTS: ALOE VERA LEAF JUICE; CARBOMER HOMOPOLYMER, UNSPECIFIED TYPE; cetyl alcohol; DMDM Hydantoin; glyceryl monostearate; ISOPROPYL ALCOHOL; methylparaben; mineral oil; polysorbate 20; propylparaben; water; stearic acid; TROLAMINE; edetate trisodium

Hydrocortisone Cream

Drug Facts

Active ingredient

Hydrocortisone 1%

Purpose

Antipruritic (anti-itch)

Uses

- for the temporary relief of itching associated with minor skin irritations, inflammation, and rashes due to eczema, insect bites, poison ivy, poison oak, poison sumac, soaps, detergents, cosmetics, jewelry
- and for external anal and genital itching.

Warnings

For external use only.

Avoid contact with eyes.

Do not use

- if you have a vaginal discharge. Consult a doctor

When using this product

- do not exceed the recommended daily dosage unless directed by a doctor
- do not put into the rectum by using fingers or any mechanical device or applicator

Stop use and ask a doctor if

- condition worsens
- symptoms persist for more than 7 days or clear up and occurs again within a few days
- beeding occurs

PREGNANCY OR BREAST FEEDING

If pregnant or breast-feeding, ask a health professional before use.

Keep out of reach of children. If swallowed, get medical help or contact a Poison Control Center right away: 800-222-1222.

Directions

For itching associated with minor skin irritations, inflammation, and rashes:

Adults and children 2 years of age and older:

- apply to affected area not more than 3 to 4 times daily

Children under 2 years of age: Consult a doctor

For external anal and genital itching:

Adults and children 12 years of age and older:

- when practical, cleanse the affected area with mild soap or warm water and rinse thoroughly or by patting or blotting with an appropriate cleansing pad
- gently dry by patting or blotting with toilet tissue or a soft cloth before application of this product
- apply to affected area not more than 3 to 4 times daily

Children under 12 years of age: Consult a doctor

Other information

- Store at 15 to 30°C (59 to 86°F)
- Tamper Evident: DO NOT USE IF SEAL ON TUBE IS BROKEN OR MISSING.

Inactive ingredients

aloe barbadensis leaf juice, carbomer, cetyl alcohol, DMDM hydantoin, glyceryl stearate, isopropyl alcohol, methylparaben, mineral oil, polysorbate-20, propylparaben, purified water, stearic acid, triethanolamine, trisodium EDTA

Questions or comments?

866-323-0107 or www.natureplex.com

PRINCIPAL DISPLAY PANEL - 28 g Tube Carton

Natureplex™

MAXIMUM STRENGTH
Hydrocortisone
Cream

FAST
ITCH & RASH
RELIEF

Net Wt. 1.5 oz. (28g)